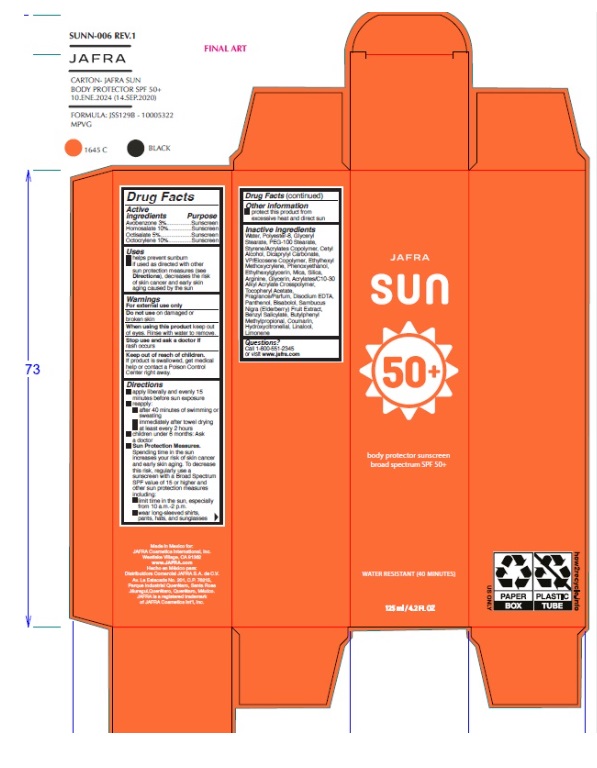 DRUG LABEL: Jafra Sun body protector sunscreen broad spectrum SPF 50
NDC: 68828-294 | Form: CREAM
Manufacturer: Distribuidora Comercial Jafra, S.A. de C.V.
Category: otc | Type: HUMAN OTC DRUG LABEL
Date: 20250122

ACTIVE INGREDIENTS: AVOBENZONE 3 g/100 mL; HOMOSALATE 10 g/100 mL; OCTOCRYLENE 10 g/100 mL; OCTISALATE 5 g/100 mL
INACTIVE INGREDIENTS: GLYCERYL MONOSTEARATE; GLYCERIN; ETHYLHEXYLGLYCERIN; PHENOXYETHANOL; POLYESTER-8 (1400 MW, CYANODIPHENYLPROPENOYL CAPPED); EUROPEAN ELDERBERRY; .ALPHA.-TOCOPHEROL ACETATE; VINYLPYRROLIDONE/EICOSENE COPOLYMER; WATER; CARBOMER COPOLYMER TYPE B (ALLYL PENTAERYTHRITOL CROSSLINKED); PEG-100 STEARATE; PANTHENOL; ARGININE; CETYL ALCOHOL; EDETATE DISODIUM; MICA; ETHYLHEXYL METHOXYCRYLENE; LEVOMENOL; DICAPRYLYL CARBONATE; BENZYL SALICYLATE; BUTYLPHENYL METHYLPROPIONAL; COUMARIN; HYDROXYCITRONELLAL; LIMONENE, (+)-; LINALOOL, (+/-)-; SILICON DIOXIDE

Jafra Sun body protector sunscreen broad spectrum SPF 50+

ACTIVE INGREDIENT

Avobenzone 3%..............Sunscreen

Homosalate 10%.............Sunscreen

Octisalate 5%..................Sunscreen

Octocrylene 10%.............Sunscreen

Uses

- helps prevent sunburn
- if used as directed with other sun protection measures (see Directions), decreases the risk of skin cancer and early skin aging caused by the sun

Warnings

For external use only

Do not use on damaged or broken skin

When using this product keep out of eyes. Rinse with water to remove.

Stop use and ask a doctor if rash occurs

Keep out of reach of children. If product is swallowed, get medical help or contact a Poison Control Center right away.

Directions

- apply liberally and evenly 15 minutes before sun exposure
- Reapply:
  • after 40 minutes of swimming or sweating
  • immediately after towel drying
  • at least every 2 hours
- children under 6 months of age : Ask a doctor
- Sun Protection Measures.Spending time in the sun increases your risk of skin cancer and early skin aging. To decrease this risk, regularly use a sunscreen with a Broad Spectrum SPF value of 15 or higher and other sun protection measures including:

• limit time in the sun, especially from 10 a.m. - 2 p.m.
• wear long-sleeved shirts, pants, hats, and sunglasses

Other Information

- protect this product from excessive heat and direct sun

Inactive Ingredients

Water, Polyester-8, Glyceryl Stearate, PEG-100 Stearate, Styrene/Acrylates Copolymer, Cetyl Alcohol, Dicaprylyl Carbonate, VP/Eicosene Copolymer, Ethylhexyl Methoxycrylene, Phenoxyethanol, Ethylhexylglycerin, Mica, Silica, Arginine, Glycerin, Acrylates/C10-30 Alkyl Acrylate Crosspolymer, Tocopheryl Acetate, Fragrance/Parfum, Disodium EDTA, Panthenol, Bisabolol, Sambucus Nigra (Elderberry) Fruit Extract, Benzyl Salicylate, Butylphenyl Methylpropional, Coumarin, Hydroxycitronellal, Linalool, Limonene

Questions?

Call 1-800-551-2345 or visit www.jafra.com